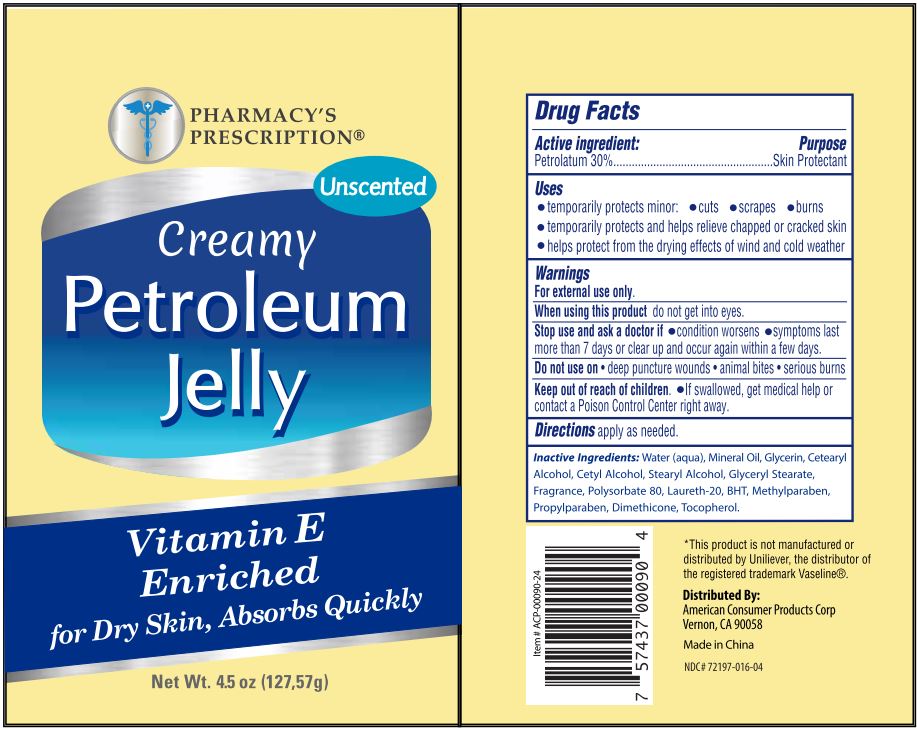 DRUG LABEL: Pharmacys Prescription 4.5 OZ Creamy Petroleum Jelly
NDC: 72197-016 | Form: JELLY
Manufacturer: American Consumer Products Corp
Category: otc | Type: HUMAN OTC DRUG LABEL
Date: 20190917

ACTIVE INGREDIENTS: PETROLATUM 30 g/100 g
INACTIVE INGREDIENTS: BUTYLATED HYDROXYTOLUENE; WATER; CETOSTEARYL ALCOHOL; CETYL ALCOHOL; GLYCERYL MONOSTEARATE; LAURETH-20; METHYLPARABEN; ALPHA-TOCOPHEROL ACETATE; MINERAL OIL; STEARYL ALCOHOL; DIMETHICONE; GLYCERIN; POLYSORBATE 80; PROPYLPARABEN

Pharmacys Prescription 4.5 OZ Creamy Petroleum Jelly

Active Ingredient

Petrolatum 30%

Purpose

Skin Protectant

Uses:

Temporarily protects minor: cuts, scrapes, burns.

Temporarily protects and helps relieve chapped or cracked skin.

Helps protect from the drying effects of wind and cold weather.

Warnings

For external use only

Keep out of reach of children

If swallowed, get medical help or contact a Poison Control Center right away.

Inactive Ingredients

Inactive Ingredients: Water (aqua), Mineral Oil, Glycerin, Cetearyl Alcohol, Cetyl Alcohol, Stearyl Alcohol, Glyceryl Stearate, Fragrance, Polysorbate 80, Laureth-20, BHT, Methylparaben, Propylparaben, Dimethicone, Tocopherol.

Directions

Directions apply as needed.

Do not use on deep puncture wounds, animal bites, serious burns.

Stop use and ask a doctor if condition worsens, symptoms last more than 7 days or clear up and occur again within a few days.

Indications & Usage

When using this product do not get into eyes.